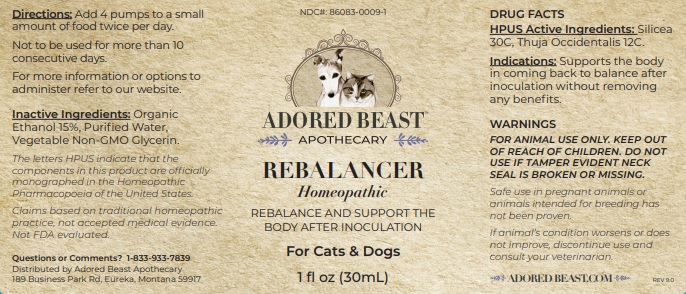 DRUG LABEL: REBALANCER
NDC: 86083-0009 | Form: LIQUID
Manufacturer: The Adored Beast Apothecary, Ltd
Category: homeopathic | Type: OTC ANIMAL DRUG LABEL
Date: 20251027

ACTIVE INGREDIENTS: SILICON DIOXIDE 30 [hp_C]/30 mL; THUJA OCCIDENTALIS LEAFY TWIG 12 [hp_C]/30 mL
INACTIVE INGREDIENTS: ALCOHOL; WATER; glycerin

REBALANCER

DRUG FACTS
HPUS Active Ingredients: Silicea 30C, Thuja Occidentalis 12C.

The letters HPUS indicate that the components in this product are officially monographed in the Homeopathic Pharmacopoeia of the United States. Claims based on traditional homeopathic practice, not accepted medical evidence. Not FDA evaluated.

INDICATIONS AND USAGE

Indications: Supports the body in coming back to balance after inoculation without removing any benefits.

WARNINGS
FOR ANIMAL USE ONLY. KEEP OUT
OF REACH OF CHILDREN. DO NOT
USE IF TAMPER EVIDENT NECK
SEAL IS BROKEN OR MISSING.
Safe use in pregnant animals or
animals intended for breeding has
not been proven.

If animal’s condition worsens or does
not improve, discontinue use and
consult your veterinarian

KEEP OUT OF REACH OF CHILDREN

DOSAGE AND ADMINISTRATION

Directions: Add 4 pumps to a small amount of food twice per day. Not to be used for more than 10 consecutive days.

For more information or options to administer refer to our website.

INACTIVE INGREDIENT

Inactive Ingredients: Organic Ethanol 15%, Purified Water, Vegetable Non-GMO Glycerin.

Questions or Comments? 1-833-933-7839

Distributed by Adored Beast Apothecary

189 Business Park Rd, Eureka, Montana 59917

OTHER SAFETY INFORMATION

Safe use in pregnant animals or animals intended for breeding has not been proven.
If animal’s condition worsens or does not improve, discontinue use and consult your veterinarian

PACKAGE LABEL

NDC#: 86083-0009-1

ADORED BEAST

APOTHECARY

REBALANCER

Homeopathic

REBALANCE AND SUPPORT THE BODY AFTER INOCULATION

For Cats & Dogs

1 fl oz (30mL)

PURPOSE

Supports the body in coming back to balance after inoculation without removing any benefits.